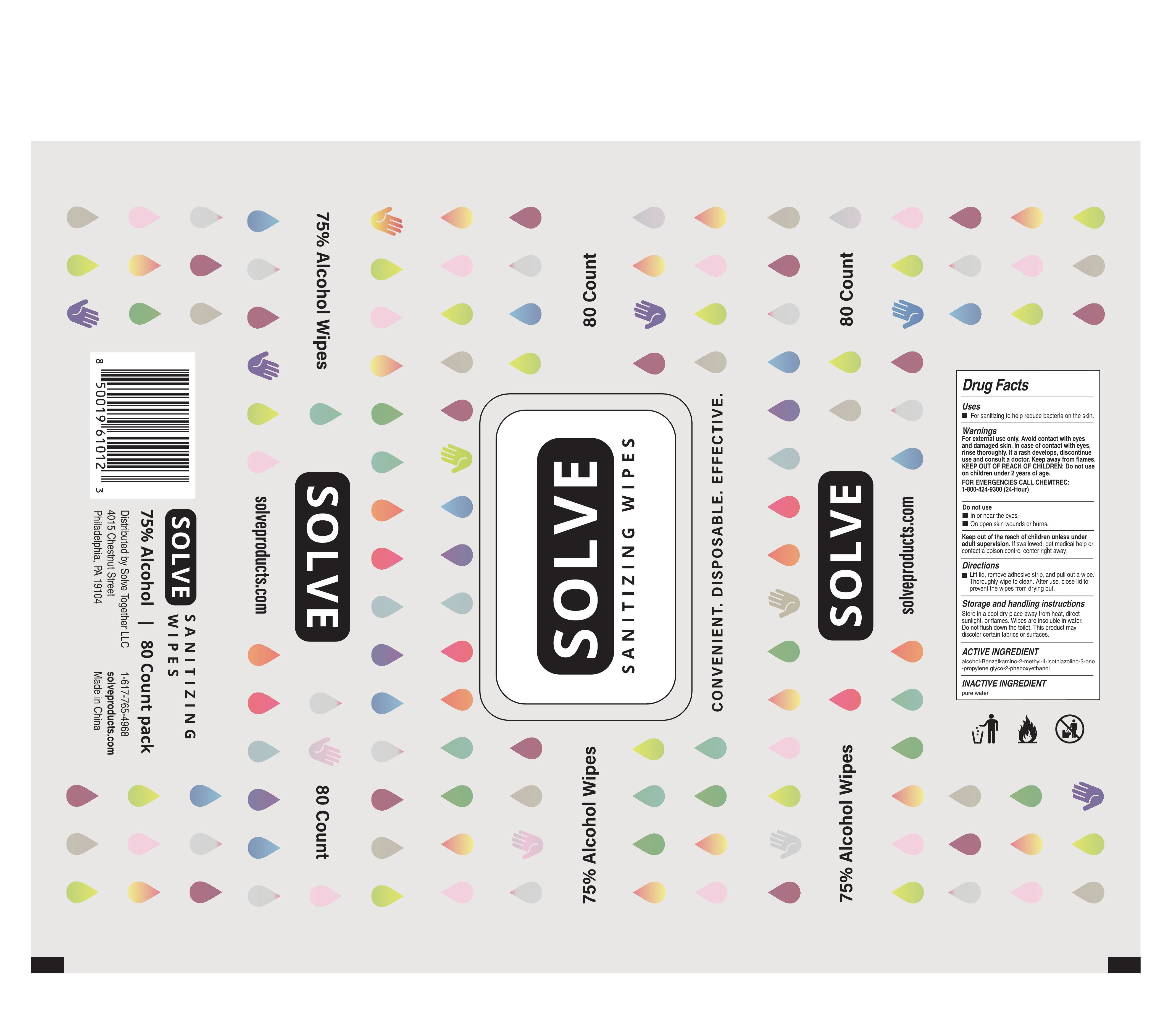 DRUG LABEL: Alcohol disinfectant wipes
NDC: 41546-017 | Form: CLOTH
Manufacturer: Zhejiang Huanghua Biological Technology Co., Ltd
Category: otc | Type: HUMAN OTC DRUG LABEL
Date: 20201207

ACTIVE INGREDIENTS: ALCOHOL 230 mL/80 1; BENZALKONIUM CHLORIDE 0.5 g/80 1; METHYLISOTHIAZOLINONE 0.5 g/80 1; PROPYLENE GLYCOL 0.5 g/80 1; PHENOXYETHANOL 0.5 g/80 1
INACTIVE INGREDIENTS: WATER

DOSAGE AND ADMINISTRATION

Store in a cool dry place away from heat, direct sunlight, or flames.

INACTIVE INGREDIENT

pure water

INDICATIONS AND USAGE

Lift lid, remove adhesive strip, and pull out a wipe.Thoroughly wipe to clean.After use, close lid to prevent the wipes from drying out.

ACTIVE INGREDIENT

alcohol

Benzalkamine

2-methyl-4-isothiazoline-3-one

propylene glyco

2-phenoxyethanol

DO NOT USE

ln or near the eyes.
On open skin wounds or burns.

KEEP OUT OF REACH OF CHILDREN

Keep out of the reach of children unless under aduit supervision. If swallowed, get medical help orcontact a poison control center right away.

PURPOSE

Disinfection
Sterilization
No Rinseing

WARNINGS

For external use only. Avoid contact with eyesand damaged skin. In case of contact with eyes,rinse thoroughly. lf a rash develops, discontinue use and consult a doctor. Keep away from flames.